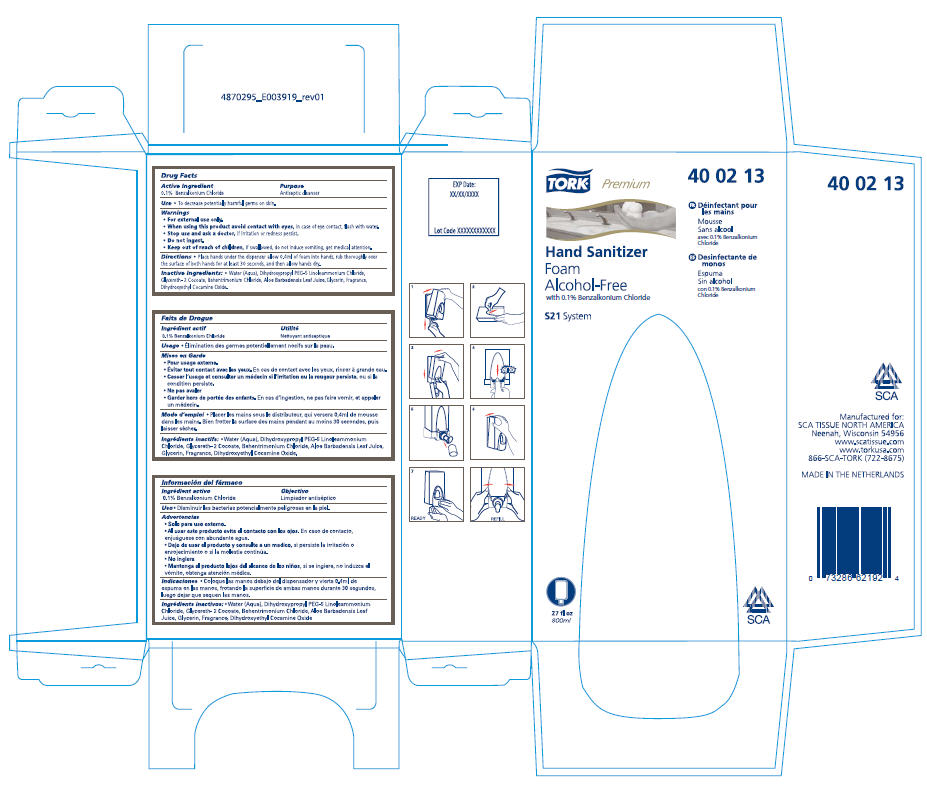 DRUG LABEL: Tork Premium Hand Sanitizer Foam Alcohol-Free
NDC: 49351-016 | Form: LIQUID
Manufacturer: SCA Tissue North America
Category: otc | Type: HUMAN OTC DRUG LABEL
Date: 20100329

ACTIVE INGREDIENTS: Benzalkonium Chloride 0.1 g/100 mL
INACTIVE INGREDIENTS: Water; Dihydroxypropyl PEG-5 Linoleammonium Chloride; Glycereth-2 Cocoate; Behentrimonium Chloride; Dihydroxyethyl Cocamine Oxide; Aloe Vera Leaf; Glycerin

TORK®
Hand Sanitizer
Foam
Alcohol-Free

Drug Facts

Active Ingredient

0.1% Benzalkonium Chloride

Purpose

Antiseptic cleanser

Use

- To decrease potentially harmful germs on skin.

Warnings

- For external use only.
- When using this product avoid contact with eyes, in case of eye contact, flush with water.
- Stop use and ask a doctor, if irritation or redness persist.
- Do not ingest.
- Keep out of reach of children, if swallowed, do not induce vomiting, get medical attention.

Directions

- Place hands under the dispenser allow 0.4ml of foam into hands, rub thoroughly over the surface of both hands for at least 30 seconds, and then allow hands dry.

Inactive Ingredients

- Water (Aqua), Dihydroxypropyl PEG-5 Linoleammonium Chloride, Glycereth- 2 Cocoate, Behentrimonium Chloride, Aloe Barbadensis Leaf Juice, Glycerin, Fragrance, Dihydroxyethyl Cocamine Oxide.

Manufactured for:
SCA TISSUE NORTH AMERICA
Neenah, Wisconsin 54956
www.scatissue.com
www.torkusa.com
866-SCA-TORK (722-8675)

PRINCIPAL DISPLAY PANEL - 800 mL Bag Carton

TORK®
Premium
40 02 13

Hand Sanitizer
Foam
Alcohol-Free
with 0.1% Benzalkonium Chloride

S21 System

FR Déinfectant pour
les mains

Mousse
Sans alcool
avec 0.1% Benzalkonium
Chloride

ES Desinfectante de
monos

Espuma
Sin alcohol
con 0.1% Benzalkonium
Chloride

27 fl oz
800ml

SCA